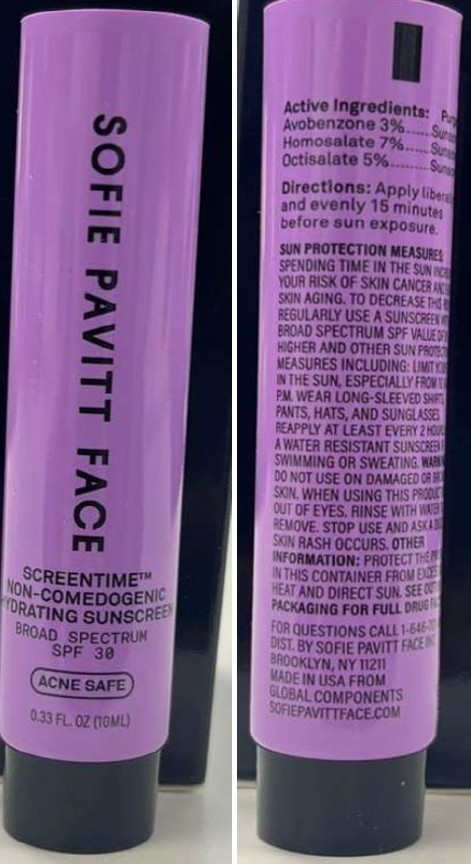 DRUG LABEL: SOFIE PAVITT FACE SPF 30
NDC: 68577-234 | Form: CREAM
Manufacturer: COSMAX USA., CORP
Category: otc | Type: HUMAN OTC DRUG LABEL
Date: 20260301

ACTIVE INGREDIENTS: AVOBENZONE 3 mg/100 mL; OCTISALATE 5 mg/100 mL; HOMOSALATE 7 mg/100 mL
INACTIVE INGREDIENTS: CITRIC ACID; CLOVE; PHENOXYETHANOL; SODIUM POLYACRYLOYLDIMETHYL TAURATE; BISABOLOL; ECTOIN; WATER; PROPANEDIOL; SILICA; XANTHAN GUM; C12-15 ALKYL BENZOATE; BUTYLOCTYL SALICYLATE; TRISODIUM ETHYLENEDIAMINE DISUCCINATE; 1,2-HEXANEDIOL; .ALPHA.-TOCOPHEROL ACETATE, D-; ETHYLHEXYLGLYCERIN; INULIN LAURYL CARBAMATE; GLYCERIN; PENTYLENE GLYCOL; ALLANTOIN; NIACINAMIDE; ETHYLHEXYL METHOXYCRYLENE

SOFIE PAVITT FACE SPF 30 (10ml)

ACTIVE INGREDIENTS:

Avobenzone 3.00%
Homosalate 7.00%
Octisalate 5.00%

Purpose

Sunscreen

USES

Use

- Help prevent sunburn
- If used as directed with other sun protection measures (see Directions) decreases the risk of skin cancer and early skin aging caused by the sun

Warnings

Do not use

- on damaged or broken skin

When using this product

- keep out of eyes. Rinse with water to remove

Stop use and ask a doctor if

- skin rash occurs

Keep out of reach of children.

DIRECTIONS

- Apply liberally and evenly15 minutes before sun exposure.
- Children under 6 months of age:Ask a doctor.
- SunProtectionMeasures. Spending time inthe sun increases your risk of skin cancer and early skin aging.To decrease this risk,regularty use a sunscreen with abroad spectrum SPFvalue of 15 or highe rand other sun protection measures including:
- limit your time in the sun,especially from 10a.m.-2p.m.
- wearlong-sleeved shirts,pants,hats,and sunglasses.
- Reapply at least every 2 hours
- Use a water resistant sunscreen if swimming or sweating.

Other information

Protect the product in this container from excessive heat and direct sun.

Inactive Ingredients

Water, C12-15 Alkyl Benzoate,Glycerin, Butyloctyl Salicylate, Niacinamide, Propanediol, Pentylene Glycol Ectoin, Eugenia Caryophyllus (Clove) Bud Extract,Solidago Virgaurea (Goldenrod) Extract, Allantoin, Bisabolol, Tocopheryl Acetate, lnulin lauryl Carbamate, Sodium Polyacryloyldimethyl Taurate, Trisodium Ethylenediamine Disuccinate, Xanthan Gum,Silica,Ethylhexyl Methoxycrylene, 1,2-Hexanediol,Citric Acid,Ethylhexylglycerin, Phenoxyethanol.

PACKAGE LABEL

NDC 6877-234